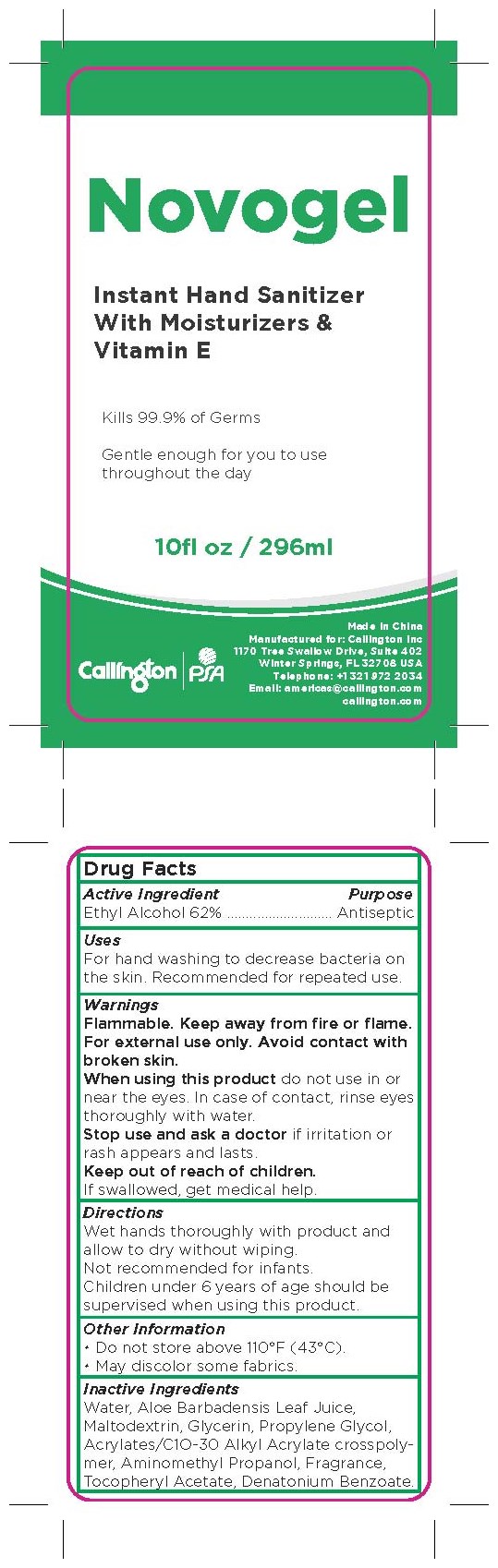 DRUG LABEL: Hand Sanitizer
NDC: 79734-010 | Form: GEL
Manufacturer: Callington Inc.
Category: otc | Type: HUMAN OTC DRUG LABEL
Date: 20200724

ACTIVE INGREDIENTS: ALCOHOL 62 mL/100 mL
INACTIVE INGREDIENTS: MALTODEXTRIN; ALOE VERA LEAF; WATER; GLYCERIN; PROPYLENE GLYCOL; CARBOMER COPOLYMER TYPE A (ALLYL PENTAERYTHRITOL CROSSLINKED); AMINOMETHYLPROPANOL; DENATONIUM BENZOATE; .ALPHA.-TOCOPHEROL ACETATE

Active Ingredient

Ethyl Alcohol 62%

Purpose

Antiseptic

Uses

For hand washing to decrease bacteria on the skin. Recommended for repeated use.

Warnings

Flammable. Keep away from fire or flame. For external use only. Avoid contact with broken skin.

When using this product do not use in or near the eyes. In case of contact, rinse eyes thoroughly with water.

Stop use and ask a doctor if irritation or rash appears and lasts.

Keep out of reach of children.

If swallowed, get medical help.

Directions

Wet hands thoroughly with product and allow to dry without wiping.

Not recommended for infants.

Children under 6 years of age should be supervised when using this product.

Other Information

- Do not store above 1109F (43℃).
- May discolor some fabrics.

Inactive Ingredients

Water, Aloe Barbadensis Leaf Juice, Maltodextrin, Glycerin, Propylene Glycol, Acrylates/C1O-30 Alkyl Acrylate crosspolymer, Aminomethyl Propanol, Fragrance, Tocopheryl Acetate, Denatonium Benzoate.